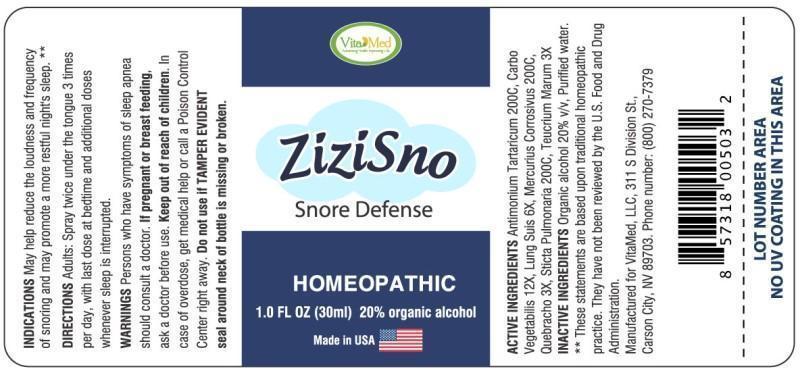 DRUG LABEL: ZIZISNO
NDC: 64249-0005 | Form: SPRAY
Manufacturer: VitaMed, LLC
Category: homeopathic | Type: HUMAN OTC DRUG LABEL
Date: 20140818

ACTIVE INGREDIENTS: ANTIMONY POTASSIUM TARTRATE 200 [hp_C]/1 mL; ACTIVATED CHARCOAL 12 [hp_X]/1 mL; SUS SCROFA LUNG 6 [hp_X]/1 mL; MERCURIC CHLORIDE 200 [hp_C]/1 mL; ASPIDOSPERMA QUEBRACHO-BLANCO BARK 3 [hp_X]/1 mL; LOBARIA PULMONARIA 200 [hp_C]/1 mL; TEUCRIUM MARUM 3 [hp_X]/1 mL
INACTIVE INGREDIENTS: WATER; ALCOHOL

DRUG FACTS

ACTIVE INGREDIENTS:

Antimonium Tartaricum 200C, Carbo Vegetabilis 12X, Lung Suis 6X, Mercurius Corrosivus 200C, Quebracho 3X, Sticta Pulmonaria 200C, Teucrium Marum 3X,

INDICATIONS:

May help reduce the loudness and frequency of snoring and may promote a more restful night's sleep. **

**These statements are based upon traditional homeopathic practice. They have not been reviewed by the U.S. Food and Drug Administration.

WARNINGS:

Persons who have symptoms of sleep apnea should consult a doctor.

If pregnant or breast feeding, ask a doctor before use.

Keep out of reach of children. In case of overdose, get medical help or call a Poison Control Center right away.

Do not use if TAMPER EVIDENT seal around neck of bottle is missing or broken.

Keep out of reach of children. In case of overdose, get medical help or call a Poison Control Center right away.

DIRECTIONS:

Adults: Spray twice under the tongue 3 times per day, with the last dose at bedtime and additional doses whenever sleep is interrupted.

INDICATIONS:

May help reduce the loudness and frequency of snoring and may promote a more restful night's sleep. **

**These statements are based upon traditional homeopathic practice. They have not been reviewed by the U.S. Food and Drug Administration.

INACTIVE INGREDIENTS:

Organic alcohol 20% v/v, Purified water.

QUESTIONS:

Manufactured for VitaMed, LLC, 311 S Division St.,

Carson City, NV 89703. Phone number: (800) 270-7379

PACKAGE LABEL DISPLAY

Vita Med

ZiziSno

Snore Defense

HOMEOPATHIC

1.0 FL OZ (30ml)